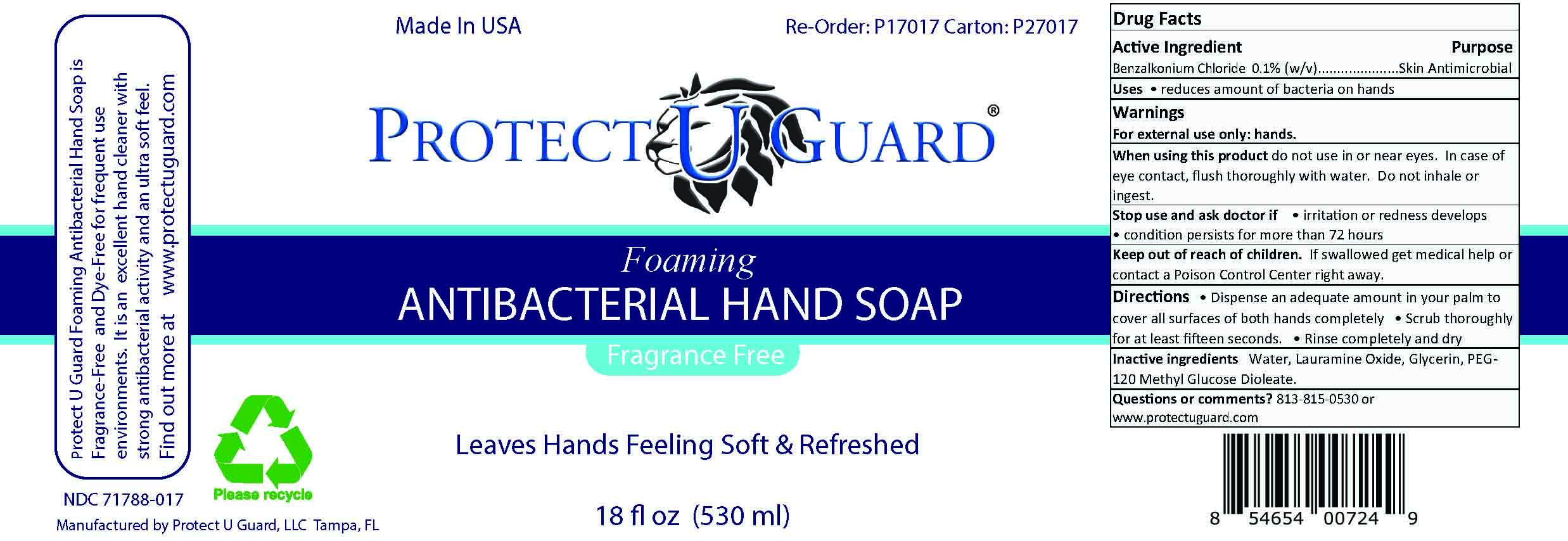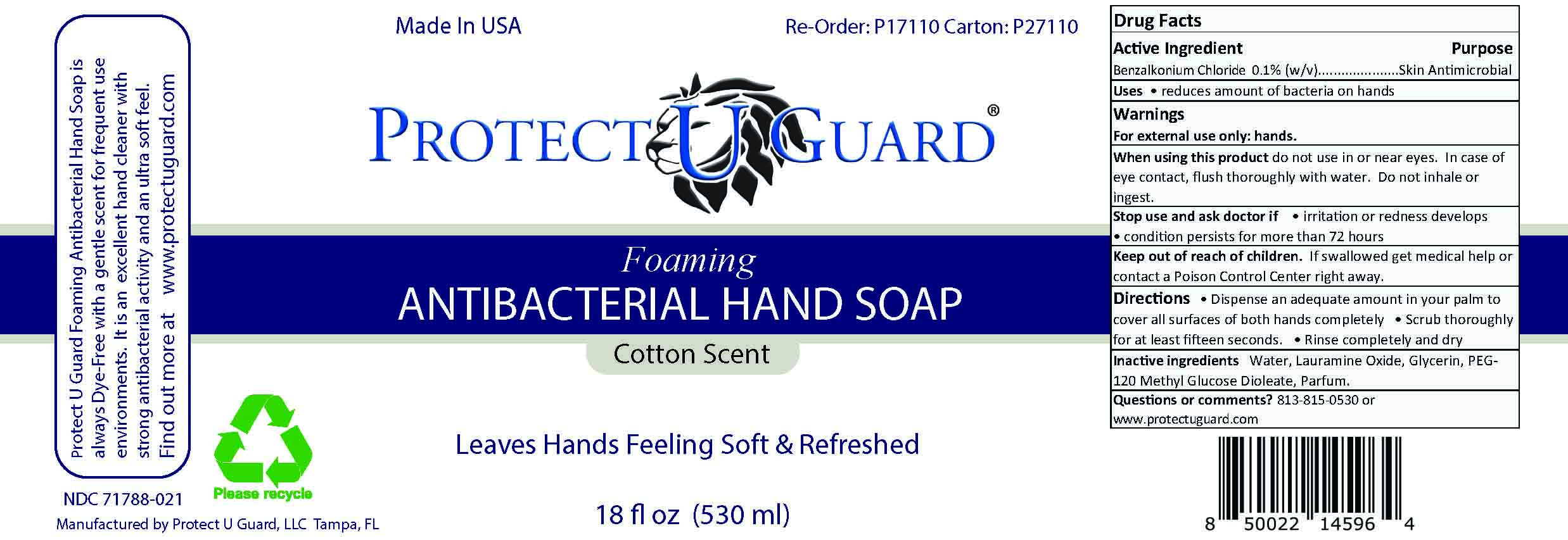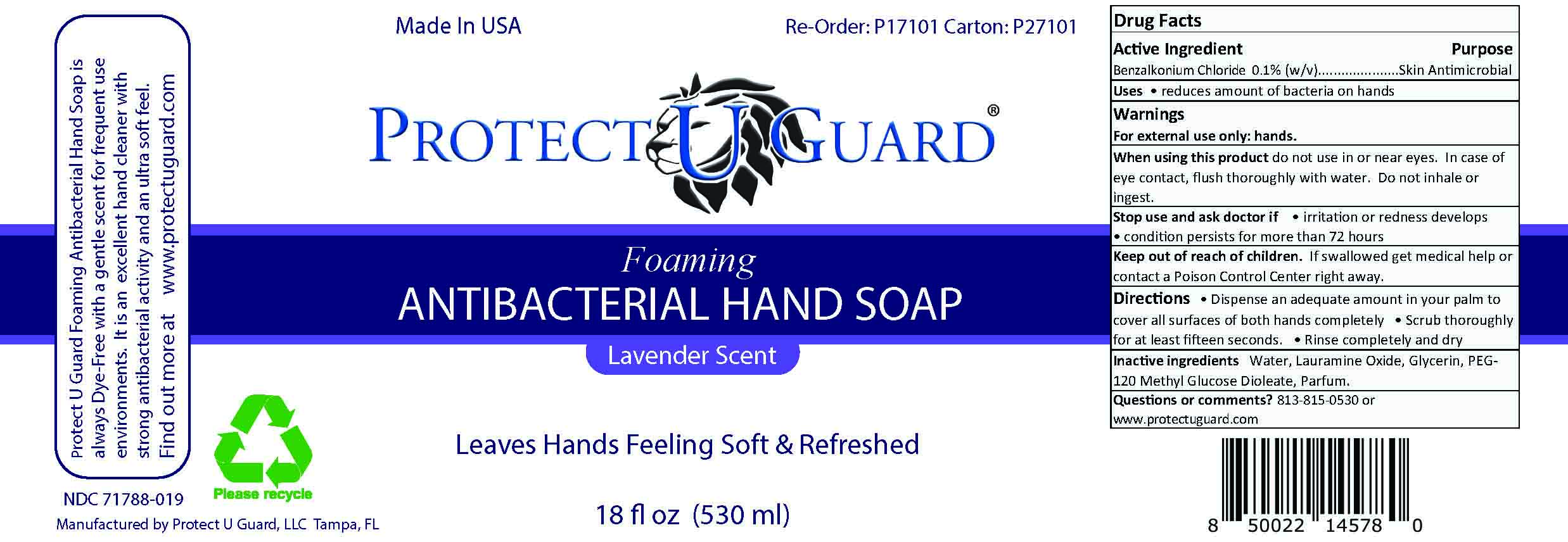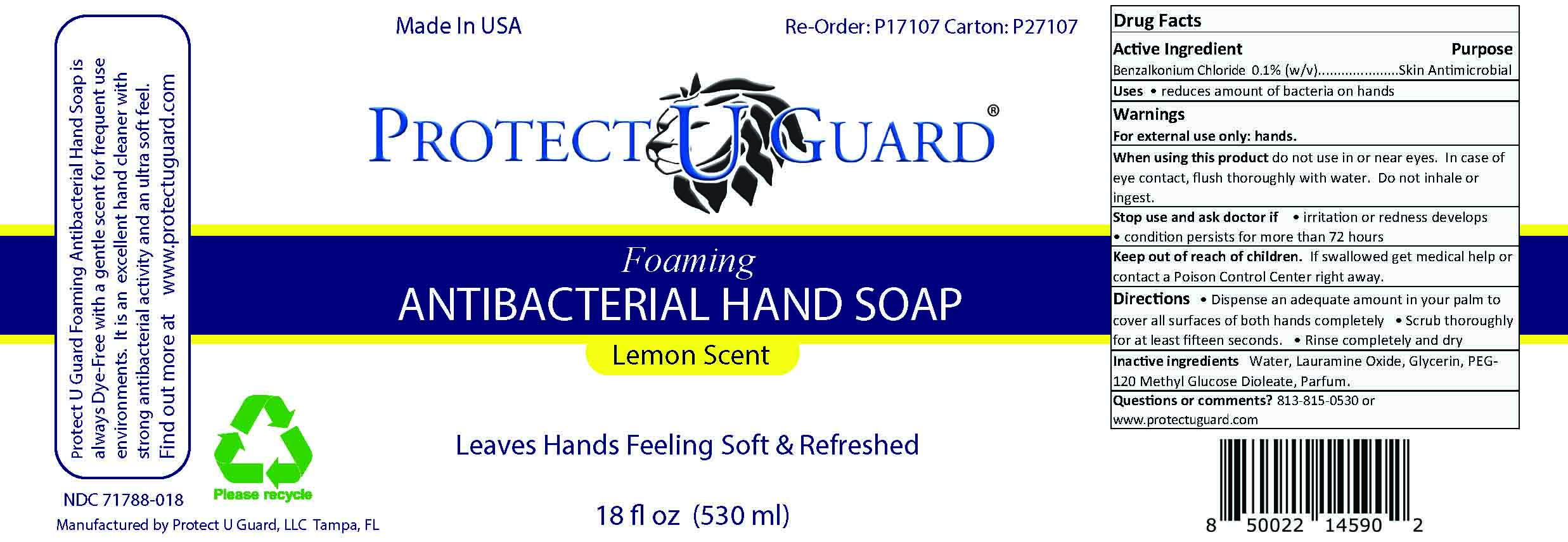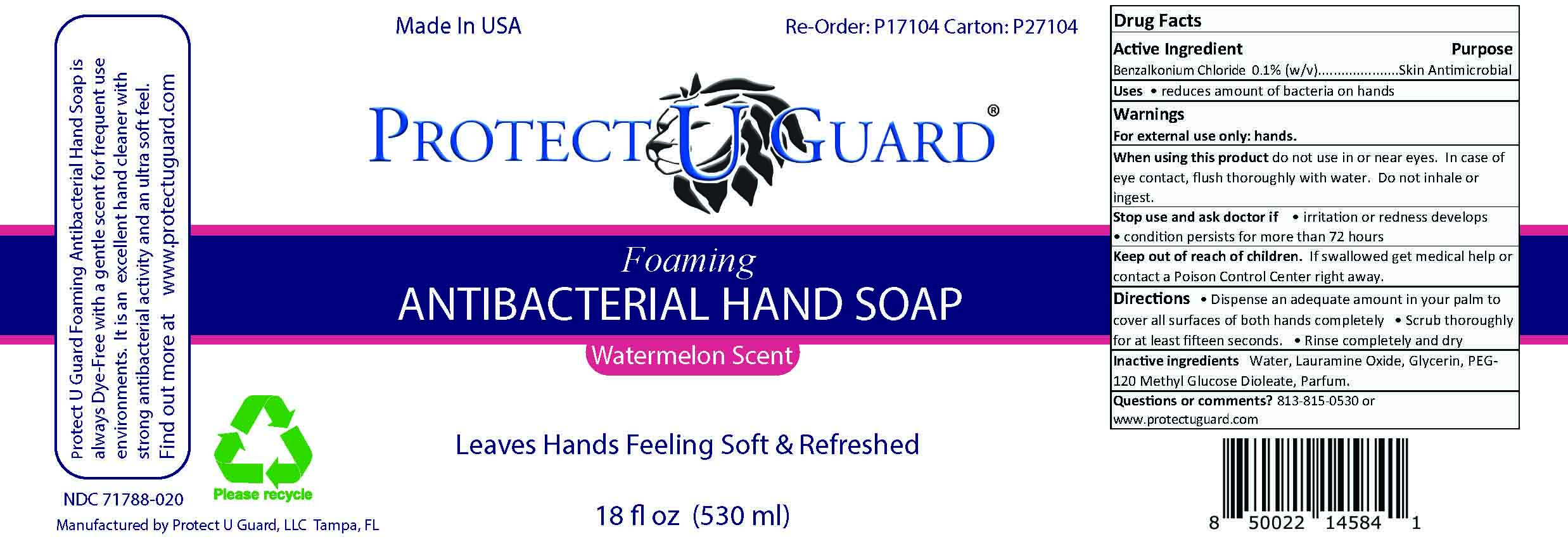 DRUG LABEL: Antibacterial Lavender Scent
NDC: 71788-019 | Form: LIQUID
Manufacturer: Protect U Guard LLC
Category: otc | Type: HUMAN OTC DRUG LABEL
Date: 20241231

ACTIVE INGREDIENTS: BENZALKONIUM CHLORIDE 0.1 g/100 mL
INACTIVE INGREDIENTS: LAURAMINE OXIDE; WATER; PEG-120 METHYL GLUCOSE DIOLEATE; GLYCERIN

Active Ingredient

Benzalkonium Chloride 0.1%

Purpose

Skin Antimicrobial

Uses

reduces amount of bacteria on hands

Warnings

For external use only: hands.

When using this product

do not use in or near eyes. In case of eye contact, flush thoroughly with water. Do not inhale or ingest.

Stop use and ask doctor if

irritation or redness develops. condition persists for more than 72 hours

Keep out of reach of children.

If swallowed get medical help or contact a Poison Control Center right away.

Directions

Dispense an adequate amount in your palm to cover all surfaces of both hands completely. Scrub thoroughly for at least fifteen seconds. Rinse completely and dry

Inactive ingredients

Water, Lauramine Oxide, Glycerin, PEG-120 Methyl Glucose Dioleate, Parfum.

Questions or comments?

813-815-0530 or www.protectuguard.com